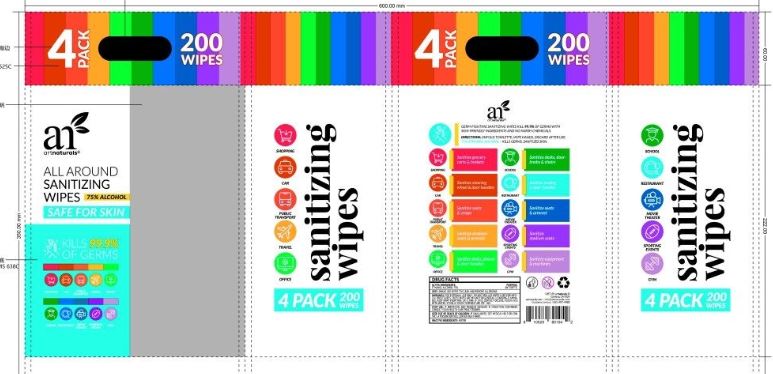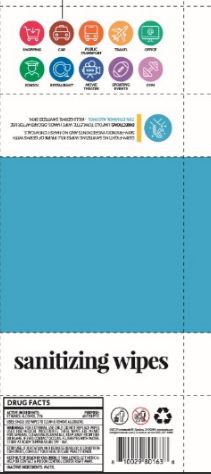 DRUG LABEL: All Around Sanitizing Wipes
NDC: 79650-050 | Form: LIQUID
Manufacturer: Zhangzhou Zhongnan Nursing Products Co., Ltd.
Category: otc | Type: HUMAN OTC DRUG LABEL
Date: 20200804

ACTIVE INGREDIENTS: ALCOHOL 75 mL/100 mL
INACTIVE INGREDIENTS: WATER

ACTIVE INGREDIENT

Ethanol Alcohol 75%

PURPOSE

Antiseptic

INDICATIONS AND USAGE

Single use wipes to clean & remove allergens

WARNINGS

For eternal use only. Do not replace wipes used for medical procedures. These wipes are meant for general cleansing. Flammable, Keep away from fire or flame. If eyes contact occurs, flush eyes with water. Store at room temperature 59F – 86F.

STOP USE

If irritation and redness develop. If condition continues, consult your health care practitioner.

KEEP OUT OF REACH OF CHILDREN

If swallowed, get medical help or contact a Poison Control Center right away.

INACTIVE INGREDIENT

Water (aqua)

Directions

Supervise children under 6 years of age when using this product to avoid swallowing.

50pcs and 200pcs All Around Sanitizing Wipes

50pcs All Around Sanitizing Wipes, NDC: 79650-050-08

200pcs All Around Sanitizing Wipes, NDC: 79650-050-09